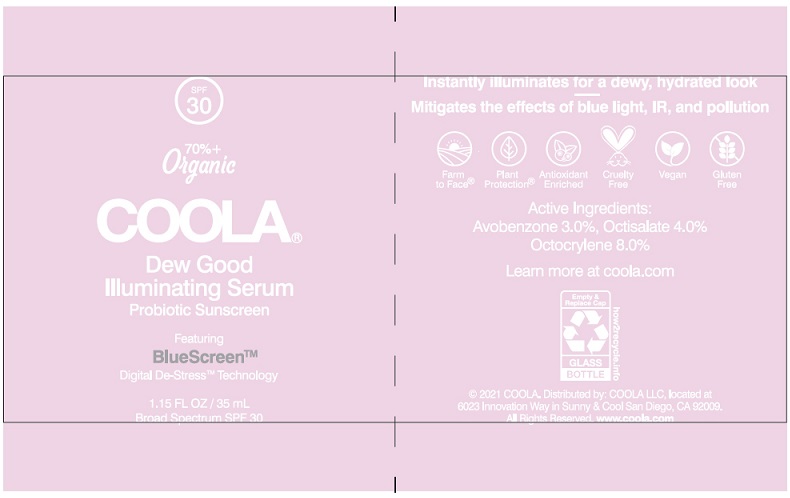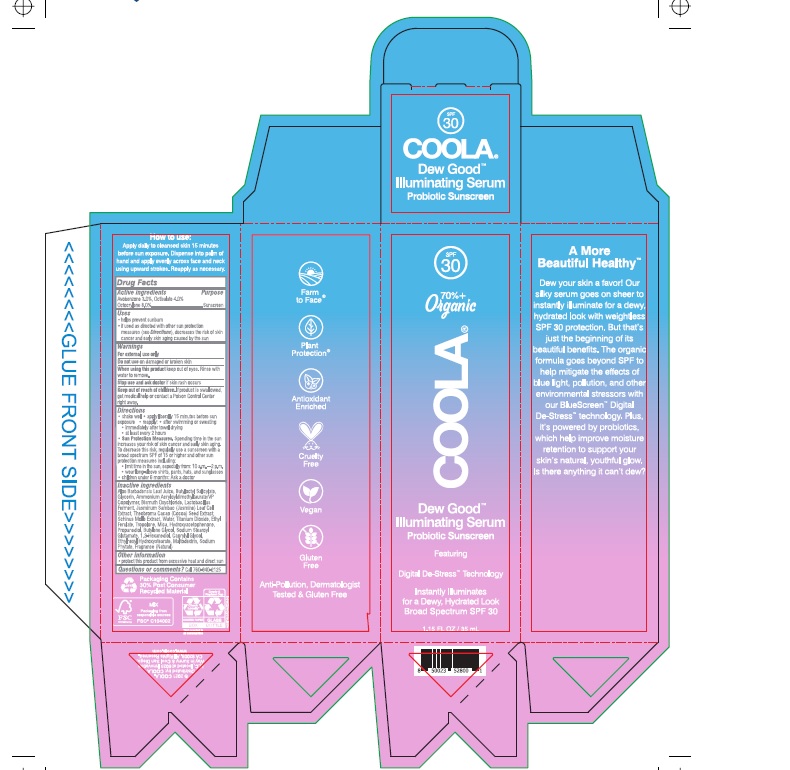 DRUG LABEL: Dew Good Illuminating Serum
NDC: 79753-034 | Form: LOTION
Manufacturer: COOLA
Category: otc | Type: HUMAN OTC DRUG LABEL
Date: 20211226

ACTIVE INGREDIENTS: AVOBENZONE 3.0 g/100 mL; OCTISALATE 4.0 mg/100 mL; OCTOCRYLENE 8.0 mg/100 mL
INACTIVE INGREDIENTS: ALOE VERA LEAF; BUTYLOCTYL SALICYLATE; GLYCERIN; AMMONIUM ACRYLOYLDIMETHYLTAURATE/VP COPOLYMER; BISMUTH OXYCHLORIDE; LACTOBACILLUS FERMENTUM; JASMINUM SAMBAC FLOWER; COCOA; SCHINUS MOLLE FRUITING TOP; WATER; TITANIUM DIOXIDE; ETHYL FERULATE; TROPOLONE; MICA; HYDROXYACETOPHENONE; PROPANEDIOL; BUTYLENE GLYCOL; SODIUM STEAROYL GLUTAMATE; 1,2-HEXANEDIOL; CAPRYLYL GLYCOL; ETHYLHEXYL HYDROXYSTEARATE; MALTODEXTRIN; PHYTATE SODIUM

COOLA Dew Good Illuminating Serum Probiotic Sunscreen SPF 30

DRUG FACTS

Active Ingredients
Avobenzone 3.0%, Octisalate 4.0%, Octocrylene 8.0%

Purpose
Sunscreen

Uses
• helps prevent sunburn
• if used as directed with other sun protection measures
(see Directions) decreases the risk of skin cancer and
early skin aging caused by the sun

Warnings
For external use only

Do not use on damaged or broken skin

When using this product keep out of eyes.
Rinse with water to remove.

Stop use and ask doctor if rash occurs

Keep out of reach of children. If product is swallowed
get medical help or contact a Poison Control Center right away.

Directions
• Shake well • apply liberally 15 minutes before sun exposure
• reapply:• after swimming or sweating
• immediately after towel drying
• at least every 2 hours
• Sun Protection Measures. Spending time in the sun
increases your risk of skin cancer and early skin aging. To
decrease this risk, regularly use a sunscreen with a broad
spectrum SPF of 15 or higher and after sun protection.
measures including:
• limit time in the sun, especially from 10 a.m. – 2 p.m.
• wear long-sleeve shirts, pants, hats, and sunglasses.
• Children under 6 months: Ask a doctor

Inactive Ingredients
Aloe Barbadensis Leaf Juice, Butolyctyl Salicylate,
Glycerin, Ammonium Acryloldimethyltaurate/VP
Copolymer, Bismuth Oxychloride, Lactobacillus
Ferment, Jasmine Sambach (Jasmine) Leaf Cell
Extract, Theodora Cacao (Cocoa) Seed Extract,
Schinus Molle Extract, Water, Titanium Dioxide, Ethyl
Ferulate, Tropolone, Mica, Hydroxyacetophenone,
Propanediol, Butylene Glycol, Sodium Stearoyl,
Glutamats, 1,2-Hexanediol, Caprylyl Glycol,
Ethylhexyl Hydroxystearate, Maltodextrin, Sodium
Phylate, Fragrance (Natural)

Other Information

- protect this product from excessive heat and direct sun

Questions or Comments? Call 760-940-2125

COOLA Dew Good Package Label

SPF

30

70%

Organic

COOLA®

Dew Good

Illuminating Serum

Probiotic Sunscreen

1.15 FL OZ / 35 mL

Distributed by: COOLA LLC,

Locate at 6023 Innovation Way in

Sunny and Cool San Diego, CA 92009

www.coola.com

Carton

Bottle

res